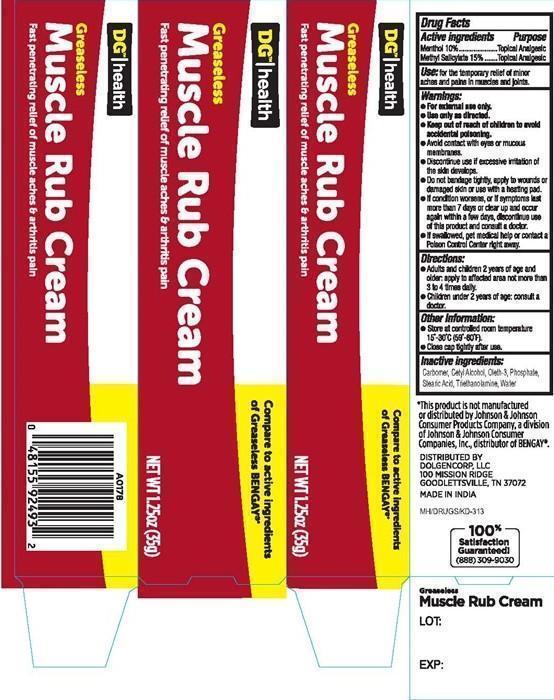 DRUG LABEL: MUSCLE RUB
NDC: 29500-2493 | Form: CREAM
Manufacturer: Personal Care Products, LLC
Category: otc | Type: HUMAN OTC DRUG LABEL
Date: 20150713

ACTIVE INGREDIENTS: MENTHOL 3.5 g/35 g; METHYL SALICYLATE 5.25 g/35 g
INACTIVE INGREDIENTS: CARBOMER HOMOPOLYMER TYPE C (ALLYL PENTAERYTHRITOL CROSSLINKED); CETYL ALCOHOL; OLETH-3; PHOSPHATE ION; STEARIC ACID; TROLAMINE; WATER

Drug Facts Active ingredients

Menthol 10%

Methyl Salicylate 15%

Purpose

Topical Analgesic

Keep out of reach of chilfren.

Keep out of reach of children to avoid accidential poisoning.

Use:

for the temporary relief of minor aches and pains in muscles and oints.

Warnings:

- For enternal use only
- Use only as directed.
- Avoid contact with eyes or mucus membranes.
- Discontinue use if excessive irritation of the skin developed.
- Do not bandage tightly, apply to wounds or damaged skin or use with a heating pad.
- If condition worsens, or if symptoms last more than 7 days or clear up and occur again within a few days, discontinue use of this product and consult a doctor.
- If swallowed, get medical help or contact a Poison Control Center right away.

Directions:

- Adults and children 2 years of age and older: apply to affected area not more than3 to 4 times daily.
- Children under 2 years of age: consult a doctor.

Inactive ingredients:

Carbomer, Cetyl Alcohol, Oleth-3, Phosphate, Stearic Acid, Triethanolamine, Water

Other information:

- Store at controlled room temperature 15°-30° (59º-80°F).
- Close cap tightly after use.

MUSCLE RUB CREAM - Product Label

DG™ l health

Greaseless Muscle Rub Cream

Fast penetrating relief of muscle aches and arthritis pain

Compare to the active ingredients of Greastless BENGAY

Net WT 1.25 oz (35G)

*This product is not manufactured or distributed by Johnsom and Johnson Consumer Products Company, a division of Johnson and Johnson Consumer Companies, Inc. distributor of BENGAY

DISTRIBUTED BY

DOLGENCORP, LLC
100 MISSION RIDGE
GOODLETTSVILLE, TN 37072

MADE IN INDIA

MH/DRUGS/KD-313

100% Satisfaction Guaranteed!

(888) 309-9030

LOT:

EXP: